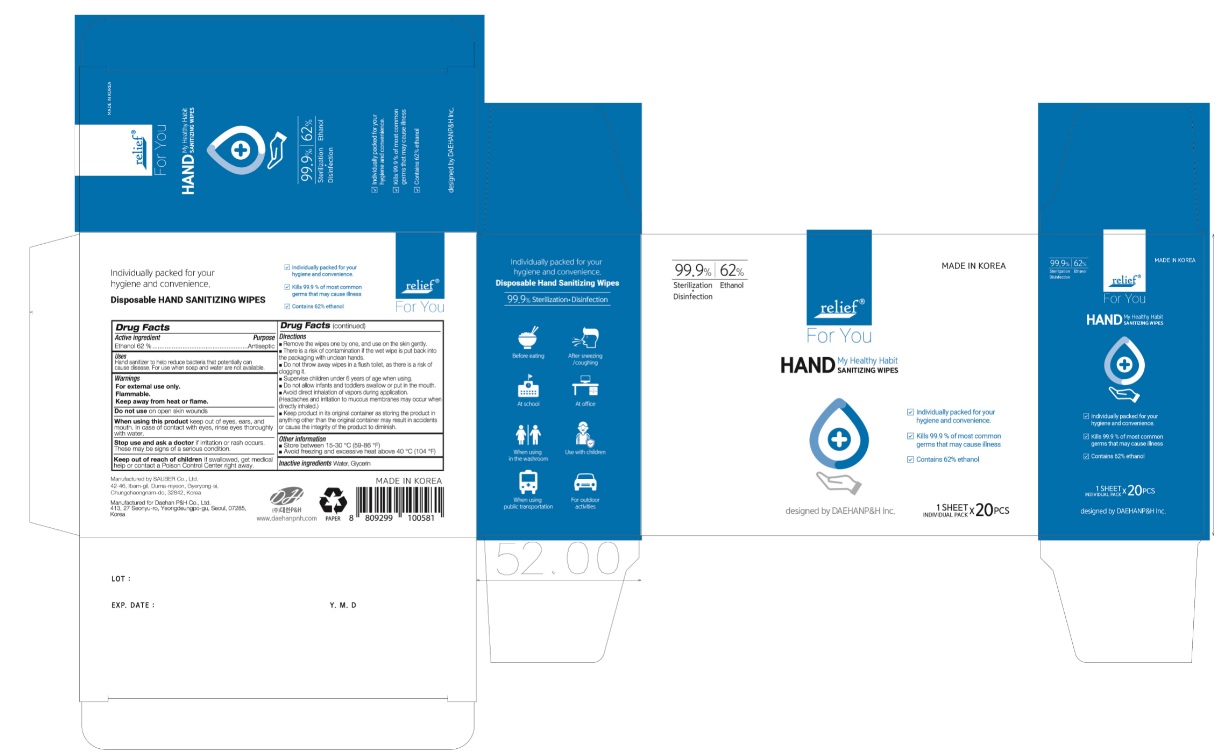 DRUG LABEL: Relief HAND SANITIZING WIPES
NDC: 79002-162 | Form: CLOTH
Manufacturer: Daehan P&H Co., Ltd.
Category: otc | Type: HUMAN OTC DRUG LABEL
Date: 20200622

ACTIVE INGREDIENTS: ALCOHOL 0.62 1/1 1
INACTIVE INGREDIENTS: GLYCERIN; WATER

Relief HAND SANITIZING WIPES | 1 ct. in 1 packet < 20 ct. in 1 box | 79002-162-20

Active Ingredient(s)

Ethanol 62% Purpose: Antiseptic

Purpose

Antiseptic

Uses

Hand sanitizer to help reduce bacteria that potentially can cause disease. For use when soap and water are not available.

Warnings

For external use only. Flammable. Keep away from heat and flame.

When using this product keep out of eyes, ears, and mouth. In case of
contact with eyes, rinse eyes thoroughly with water.

Stop use and ask a doctor if irritation or rash occurs. These may be signs of
a serious condition.

Keep out of reach of children If swallowed, get medical help or contact a
Poison Control Center right away.

Directions

■ Remove the wipes one by one, and use on the skin gently.
■ There is a risk of contamination if the wet wipe is put back into
the packaging with unclean hands.
■ Do not throw away wipes in a flush toilet, as there is a risk of
clogging it.
■ Supervise children under 6 years of age when using.
■ Do not allow infants and toddlers swallow or put in the mouth.
■ Avoid direct inhalation of vapors during application.
(Headaches and irritation to mucous membranes may occur when
directly inhaled.)
■ Keep product in its original container as storing the product in
anything other than the original container may result in accidents
or cause the integrity of the product to diminish.

Other information

■ Store between 15-30°C (59-86ºF)

■ Avoid freezing and excessive heat above 40°C (104ºF)

Inactive ingredients

Water, Glycerin